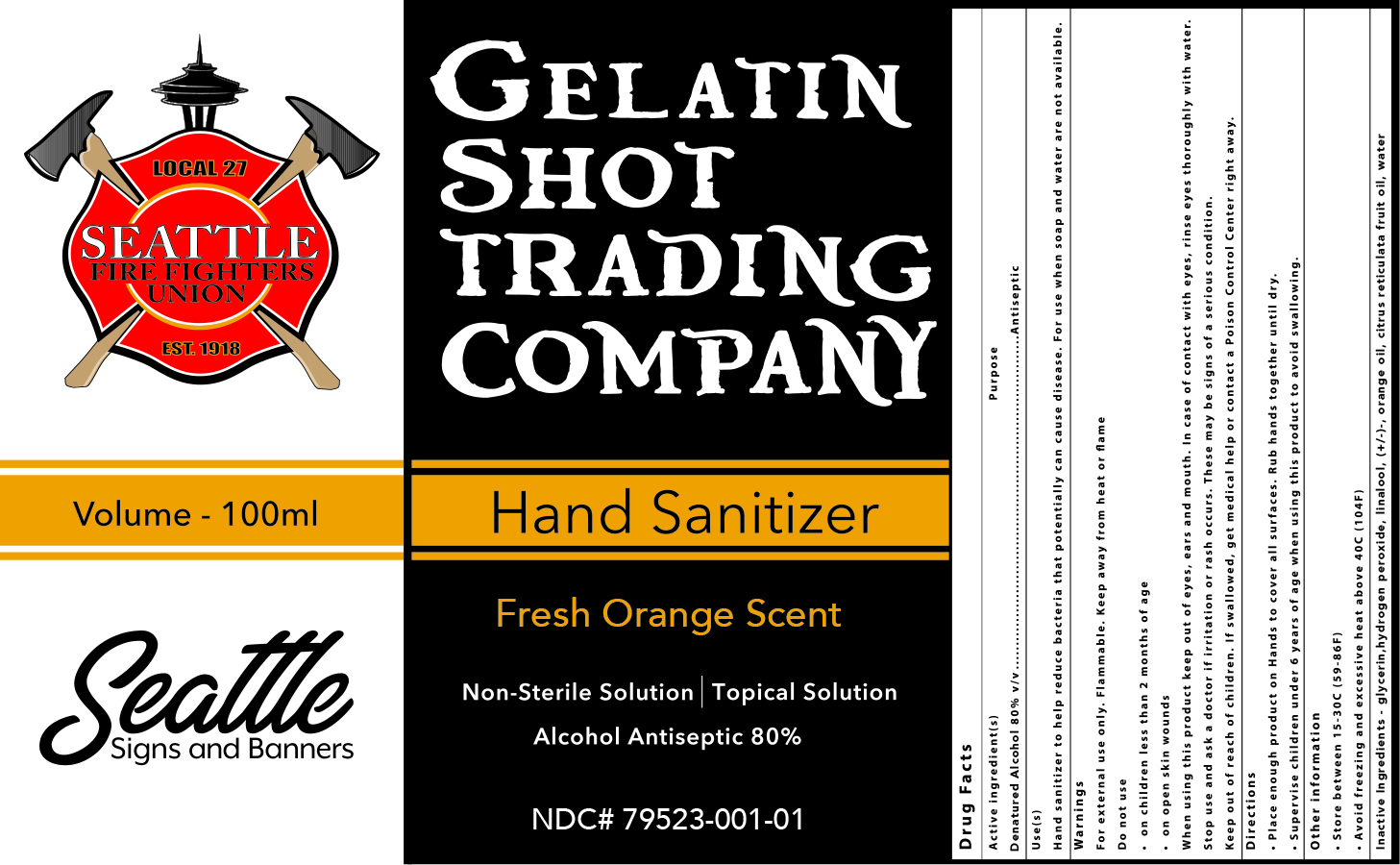 DRUG LABEL: Hand Sanitizer
NDC: 79523-001 | Form: SPRAY
Manufacturer: LaJoye Cellars
Category: otc | Type: HUMAN OTC DRUG LABEL
Date: 20201211

ACTIVE INGREDIENTS: ALCOHOL 80 mL/100 mL
INACTIVE INGREDIENTS: CITRUS RETICULATA FRUIT OIL; GLYCERIN 1.45 mL/100 mL; HYDROGEN PEROXIDE 0.125 mL/100 mL; WATER; LINALOOL, (+/-)-; ORANGE OIL

Hand Sanitizer

Active Ingredient(s)

Alcohol 80% v/v. Purpose: Antiseptic

Purpose

Antiseptic, Hand Sanitizer

Use

Hand Sanitizer to help reduce bacteria that potentially can cause disease. For use when soap and water are not available.

Warnings

For external use only. Flammable. Keep away from heat or flame

Do not use

- in children less than 2 months of age
- on open skin wounds

When using this product keep out of eyes, ears, and mouth. In case of contact with eyes, rinse eyes thoroughly with water.
Stop use and ask a doctor if irritation or rash occurs. These may be signs of a serious condition.
Keep out of reach of children. If swallowed, get medical help or contact a Poison Control Center right away.

Stop use and ask a doctor if irritation or rash occurs. These may be signs of a serious condition.

Keep out of reach of children. If swallowed, get medical help or contact a Poison Control Center right away.

Directions

- Place enough product on hands to cover all surfaces. Rub hands together until dry.
- Supervise children under 6 years of age when using this product to avoid swallowing.

Other information

- Store between 15-30C (59-86F)
- Avoid freezing and excessive heat above 40C (104F)

Inactive ingredients

GLYCERIN PDC6A3C0OX 1.45 mL

HYDROGEN PEROXIDE BBX060AN9V 0.125 mL
LINALOOL, (+/-)- D81QY6I88E
ORANGE OIL AKN3KSD11B
CITRUS RETICULATA FRUIT OIL 25P9H3QU5E
WATER 059QF0KO0R

PackageLabel Principal Display Panel

The hand sanitizer is manufactured using only the following United States Pharmacopoeia (USP) grade ingredients in the preparation of the product (percentage in final product formulation)

1. Alcohol (ethanol) (USP or Food Chemical Codex (FCC) grade) (80%, volume/volume (v/v)) in an aqueous solution denatured according to Alcohol and Tobacco Tax and Trade Bureau regulations in 27 CFR part 20.
2. Glycerol (1.45% v/v).
3. Hydrogen peroxide (0.125% v/v).
4. Sterile distilled water or boiled cold water.
5. LINALOOL, (+/-)- D81QY6I88E
6. ORANGE OIL AKN3KSD11B
7. CITRUS RETICULATA FRUIT OIL 25P9H3QU5E

Package Label - Principal Display Panel

100ML NDC#79523-001-01